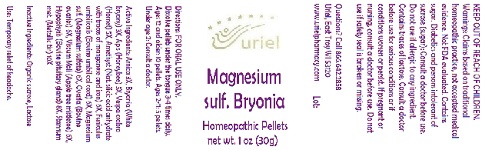 DRUG LABEL: Magnesium sulf. Bryonia
NDC: 48951-7004 | Form: PELLET
Manufacturer: Uriel Pharmacy Inc.
Category: homeopathic | Type: HUMAN OTC DRUG LABEL
Date: 20180523

ACTIVE INGREDIENTS: ARNICA MONTANA 3 [hp_X]/1 1; BRYONIA ALBA ROOT 3 [hp_X]/1 1; APIS MELLIFERA 5 [hp_X]/1 1; VESPA CRABRO 5 [hp_X]/1 1; SILICON DIOXIDE 6 [hp_X]/1 1; SUS SCROFA UMBILICAL CORD 6 [hp_X]/1 1; BOS TAURUS PITUITARY GLAND 6 [hp_X]/1 1; MAGNESIUM CATION 6 [hp_X]/1 1; BOS TAURUS OVARY 6 [hp_X]/1 1; VISCUM ALBUM FRUITING TOP 6 [hp_X]/1 1; TIN 10 [hp_X]/1 1
INACTIVE INGREDIENTS: SUCROSE

Magnesium sulf. Bryonia

INDICATIONS AND USAGE

Directions: FOR ORAL USE ONLY.

DOSAGE AND ADMINISTRATION

Dissolve pellets under the tongue 3-4 times daily. Ages 12 and older: 10 pellets. Ages 2-11: 5 pellets. Under age 2: Consult a doctor.

ACTIVE INGREDIENT

Active Ingredients: Arnica 3X, Bryonia (White bryony) 3X, Apis (Honeybee) 5X, Vespa crabro (Hornet) 5X, Amethyst (Nat. silicic acid anhydrate with traces of manganese and iron) 6X, Funiculus umbilicalis (Bovine umbilical cord) 6X, Magnesium sulf. (Magnesium sulfate) 6X, Ovaria (Bovine ovaries) 6X, Viscum Mali (Apple tree mistletoe) 6X, Hypophysis (Bovine pituitary gland) 8X, Stannum met. (Metallic tin) 10X

Inactive Ingredients: Sucrose, Lactose

PURPOSE

Use: Temporary relief of headache.

KEEP OUT OF REACH OF CHILDREN.

WARNINGS

Warnings: Claims based on traditional homeopathic practice, not accepted medical evidence. Not FDA evaluated. Contains sugar. Diabetics and persons intolerant of sucrose (sugar): Consult a doctor before use. Do not use if allergic to any ingredient. Contains traces of lactose. Consult a doctor before use for serious conditions or if conditions worsen or persist. If pregnant or nursing, consult a doctor before use. Do not use if safety seal is broken or missing.

QUESTIONS

Questions? Call 866.642.2858 Uriel, East Troy WI 53120 www.urielpharmacy.com